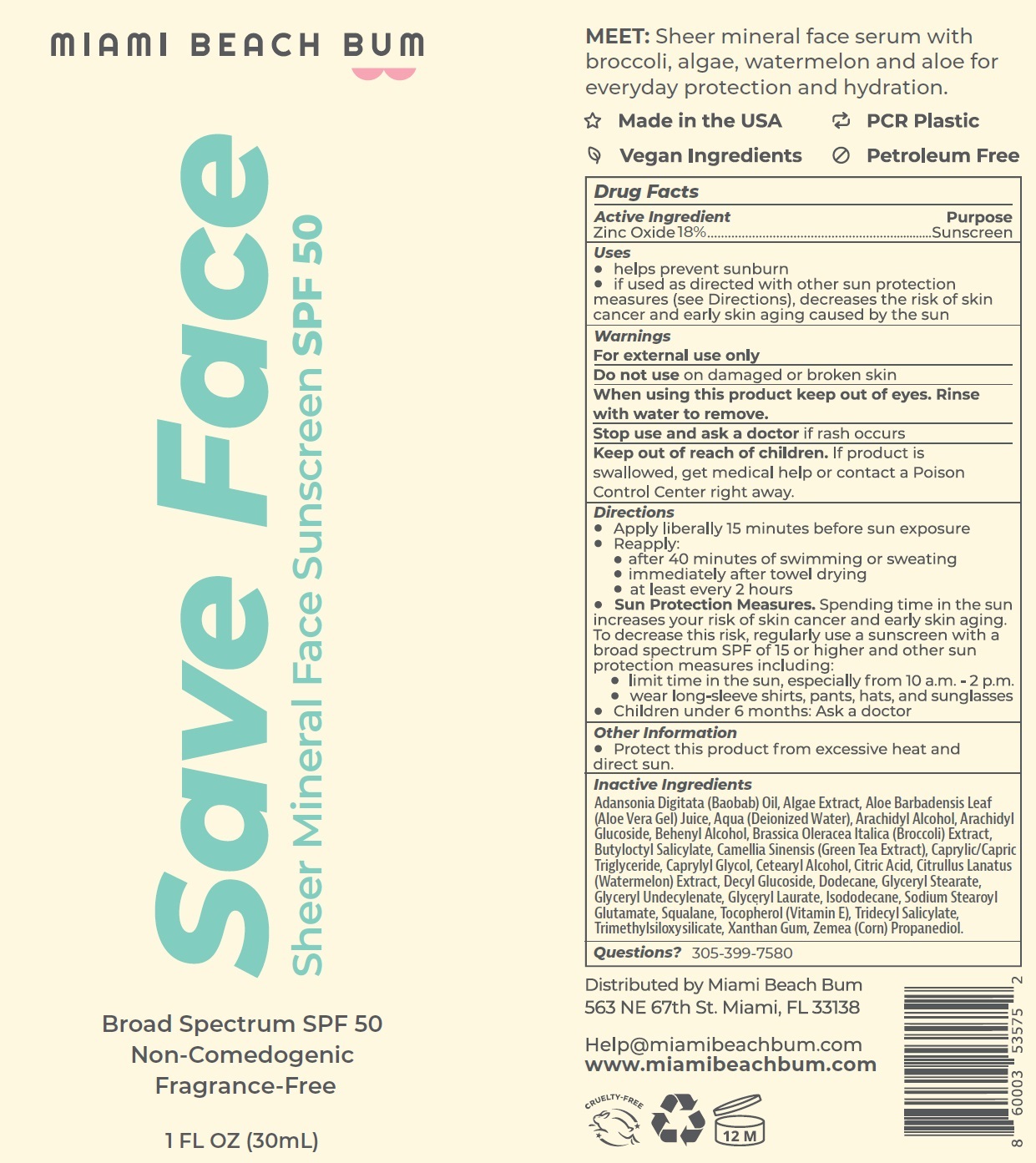 DRUG LABEL: MIAMI BEACH BUM Save Face Sheer Mineral Sunscreen SPF 50
NDC: 82812-447 | Form: CREAM
Manufacturer: MIAMI BEACH BUM
Category: otc | Type: HUMAN OTC DRUG LABEL
Date: 20240104

ACTIVE INGREDIENTS: ZINC OXIDE 180 mg/1 mL
INACTIVE INGREDIENTS: ALOE VERA LEAF; WATER; ARACHIDYL ALCOHOL; ARACHIDYL GLUCOSIDE; DOCOSANOL; BROCCOLI; BUTYLOCTYL SALICYLATE; GREEN TEA LEAF; MEDIUM-CHAIN TRIGLYCERIDES; CAPRYLYL GLYCOL; CETOSTEARYL ALCOHOL; CITRIC ACID MONOHYDRATE; WATERMELON; DECYL GLUCOSIDE; DODECANE; GLYCERYL MONOSTEARATE; GLYCERYL LAURATE; ISODODECANE; SODIUM STEAROYL GLUTAMATE; SQUALANE; .ALPHA.-TOCOPHEROL; TRIDECYL SALICYLATE; XANTHAN GUM; CORN

MIAMI BEACH BUM Save Face Sheer Mineral Sunscreen SPF-50

Active Ingredient

Zinc Oxide 18%

Purpose

Sunscreen

Uses

- helps prevent sunburn
- if used as directed with other sun protection measures (see Directions), decreases the risk of skin cancer and early skin aging caused by the sun

Warnings

For external use only

Do not use

on damaged or broken skin

When using this product

Keep out of eyes. Rinse with water to remove.

Stop use and ask a doctor

if rash occurs

Keep out of reach of children.

If product is swallowed, get medical help or contact a Poison Control Center right away.

Directions

- Apply liberally 15 minutes before sun exposure
- Reapply:
- after 40 minutes of swimming or sweating
- immediately after towel drying
- at least every 2 hours
- Sun Protection Measures.Spending time in the sun increases your risk of skin cancer and early skin aging. To decrease this risk, regularly use a sunscreen with a broad spectrum SPF of 15 or higher and other sun protection measures including:
- limit time in the sun, especially from 10 a.m. - 2 p.m.
- wear long-sleeve shirts, pants, hats, and sunglasses
- children under 6 months: Ask a doctor

Other information

- Protect this product from excessive heat and direct sun.

Inactive Ingredients

Adansonia Digitata (Baobab) Oil, Algae Extract, Aloe Barbadensis Leaf (Aloe Vera Gel) Juice, Aqua (Deionized Water), Arachidyl Alcohol, Arachidyl Glucoside, Behenyl Alcohol, Brassica Oleracea Italica (Broccoli) Extract, Butyloctyl Salicylate, Camellia Sinensis (Green Tea Extract), Caprylic/Capric Triglyceride, Caprylyl Glycol, Cetearyl Alcohol, Citric Acid, Citrullus Lanatus (Watermelon) Extract, Decyl Glucoside, Dodecane, Glyceryl Stearate, Glyceryl Undecylenate, Glyceryl Laurate, Isododecane, Sodium Stearoyl Glutamate, Squalane, Tocopherol (Vitamin E), Tridecyl Salicylate, Trimethylsiloxysilicate, Xanthan Gum, Zemea (Corn) Propanediol.

Questions?

305-399-7580